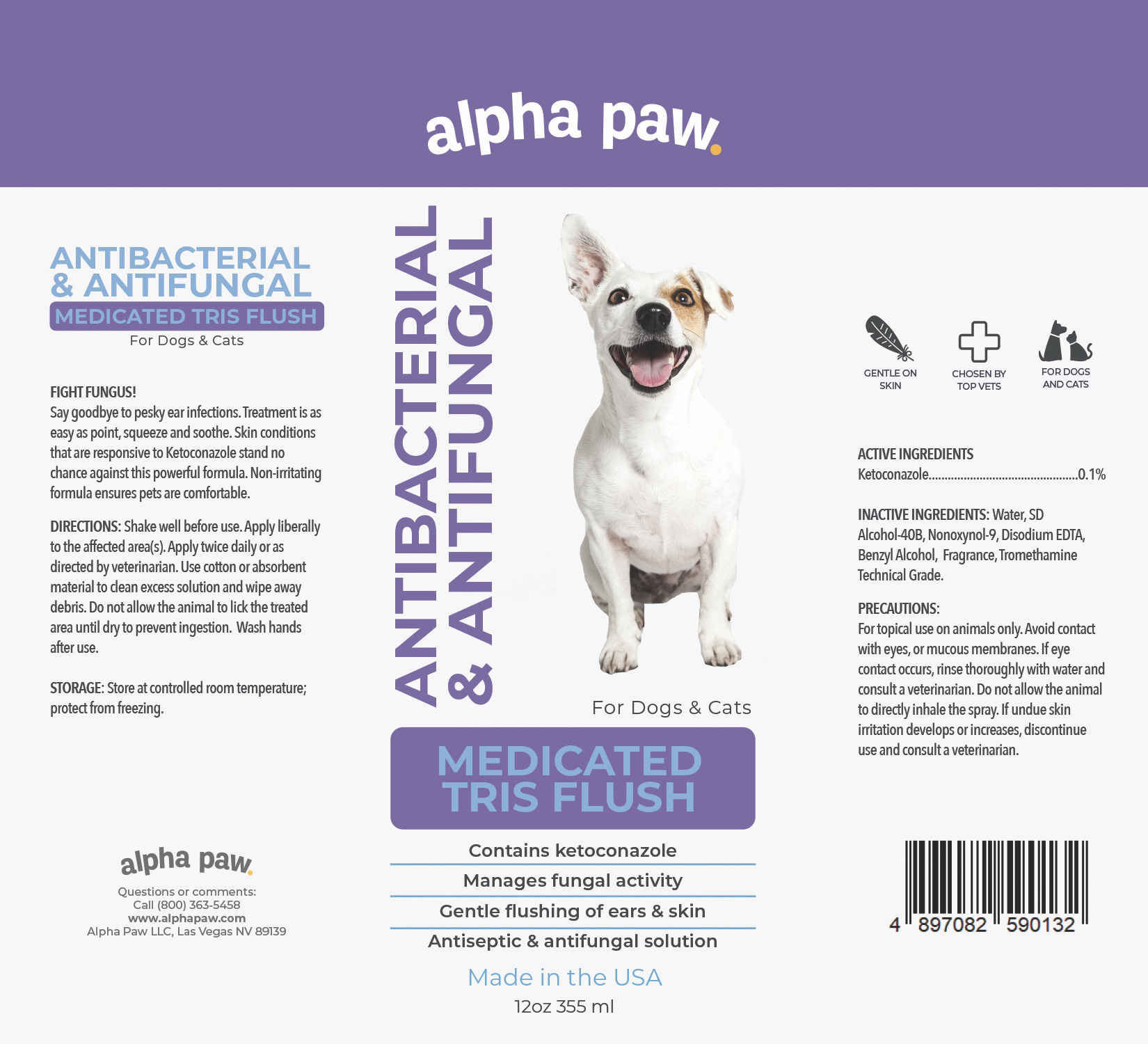 DRUG LABEL: ANTIBACTERIAL and ANTIFUNGAL MEDICATED TRIS FLUSH
NDC: 86175-005 | Form: SOLUTION
Manufacturer: Alpha Paw Inc
Category: animal | Type: OTC ANIMAL DRUG LABEL
Date: 20230322

ACTIVE INGREDIENTS: KETOCONAZOLE 0.1 g/100 mL
INACTIVE INGREDIENTS: WATER; ALCOHOL; NONOXYNOL-9; EDETATE DISODIUM ANHYDROUS; BENZYL ALCOHOL; TROMETHAMINE

ANTIBACTERIAL & ANTIFUNGAL MEDICATED TRIS FLUSH

ACTIVE INGREDIENTS
Ketoconazole...............................................0.1%

PURPOSE

ANTIBACTERIAL & ANTIFUNGAL MEDICATED TRIS FLUSH For Dogs & Cats

FIGHT FUNGUS!

Say goodbye to pesky ear infections. Treatment is as easy as point, squeeze and soothe. Skin conditions that are responsive to Ketoconazole stand no chance against this powerful formula. Non-irritating formula ensures pets are comfortable.

INACTIVE INGREDIENTS

Water, SD Alcohol-40B, Nonoxynol-9, Disodium EDTA, Benzyl Alcohol, Fragrance, Tromethamine Technical Grade.

PRECAUTIONS

For topical use on animals only. Avoid contact with eyes, or mucous membranes. If eye contact occurs, rinse thoroughly with water and consult a veterinarian. Do not allow the animal to directly inhale the spray. If undue skin irritation develops or increases, discontinue use and consult a veterinarian.

DIRECTIONS

Shake well before use. Apply liberally to the affected area(s). Apply twice daily or as directed by veterinarian. Use cotton or absorbent material to clean excess solution and wipe away debris. Do not allow the animal to lick the treated area until dry to prevent ingestion. Wash hands after use.

STORAGE

Store at controlled room temperature; protect from freezing.

Contains ketoconazole
Manages fungal activity
Gentle flushing of ears & skin
Antiseptic & antifungal solution

GENTLE ON SKIN
CHOSEN BY TOP VETS
FOR DOGS AND CATS

ALPHA PAW
Questions or Comments:
Call (800) 363-5458
www.alphapaw.com
Alpha Paw LLC, Las Vegas NV 89139

Packaging

Package 12oz 355mL